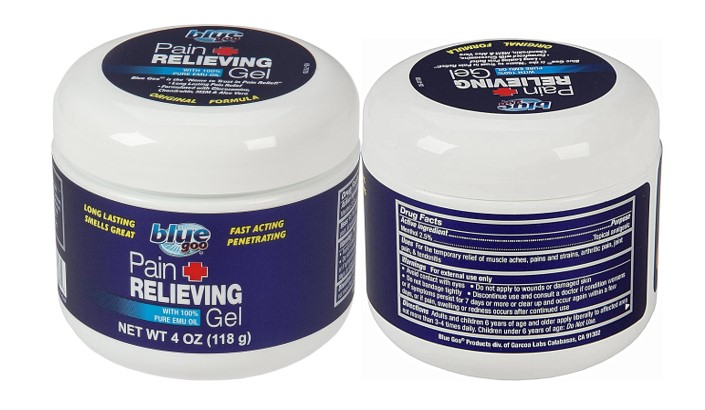 DRUG LABEL: blue goo Pain Relieving
NDC: 67385-883 | Form: GEL
Manufacturer: Garcoa, Inc.
Category: otc | Type: HUMAN OTC DRUG LABEL
Date: 20260213

ACTIVE INGREDIENTS: MENTHOL 2.5 mg/1 g
INACTIVE INGREDIENTS: WATER; DIMETHYL SULFONE; EMU OIL; DEHYDRATED ALCOHOL; GLUCOSAMINE HCL; SODIUM CHONDROITIN SULFATE (PORCINE; 5500 MW); CAMPHOR (SYNTHETIC); FEVERFEW; ARNICA MONTANA FLOWER; MATRICARIA CHAMOMILLA; URTICA DIOICA FLOWER; WITCH HAZEL; CALENDULA OFFICINALIS FLOWER; WILLOW BARK; CORIANDER; ALOE BARBADENSIS LEAF JUICE; EUCALYPTUS GLOBULUS LEAF OIL; FRAGRANCE 13576; SODIUM HYDROXIDE; CARBOMER; SORBITOL; METHYL SALICYLATE; PHENOXYETHANOL; BLUE 1

TheraCare Pain Relieving Menthol Gel

Drug Facts

Active Ingredient

Menthol 2.5%

Purpose

- Topical Analgesic

Uses

For the temporary relief of muscle aches, pains and strains, arthritic pain, joint pain, and tendonitis

Warnings

For external use only

• Avoid contact with eyes •Do not apply to wounds or damaged skin • Do not bandage tightly •Do not use with heating pads or heating devices •Discontinue use and consult a doctor if condition worsens or if symptoms persist for 7 days or more or clear up and occur again within a few days, or if pain, swelling or redness occurs after continued use

Directions

Adults and children 6 years of age and older apply liberally to affected area not more than 3-4 times daily. Children under 6 years of age: Do Not Use.

Inactive ingredients

water, dimethyl sulfone, emu oil, alcohol denat., sodium chondroitin sulfate, glucosamine HCl, camphor, chrysanthemum parthenium (Feverfew) extract, arnica montana flower extract, chamomilla recutita (Matricaria) flower extract, urtica dioica (Nettle) extract, hamamelis virginiana (Witch Hazel) extract, calendula officinalis extract, salix alba (Willow) bark extract, coriandrum sativum (Coriander) extract, aloe barbadensis leaf juice, eucalyptus globulus leaf oil, fragrance, sodium hydroxide, carbomer, sorbitol, methyl salicylate, phenoxyethanol, blue 1

Questions or comments

1-866-567-8600

PDP

Blue Goo Pain